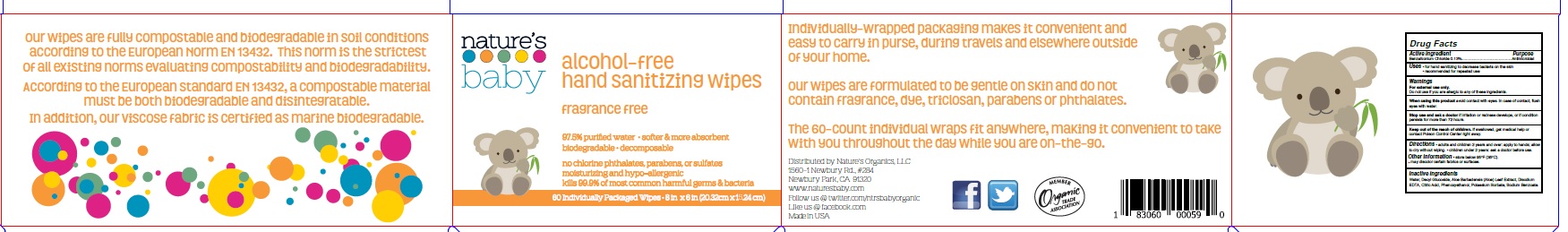 DRUG LABEL: Natures Baby
NDC: 73725-013 | Form: SWAB
Manufacturer: Nature’s Organics, LLC
Category: otc | Type: HUMAN OTC DRUG LABEL
Date: 20210108

ACTIVE INGREDIENTS: BENZALKONIUM CHLORIDE 0.13 g/100 g
INACTIVE INGREDIENTS: WATER; DECYL GLUCOSIDE; ALOE VERA LEAF; EDETATE DISODIUM ANHYDROUS; CITRIC ACID MONOHYDRATE; PHENOXYETHANOL; POTASSIUM SORBATE; SODIUM BENZOATE

Drug Facts

Active ingredient

Benzalkonium chloride 0.13%

Purpose

Antimicrobial

Uses

- For hand sanitizing to decrease bacteria on the skin
- Recommended for repeated use

Warnings

For external use only

Do not use

if you are allergic to any of these ingredients

When using this product

avoid contact with eyes. In case of contact, flush eyes with water.

Stop use and ask a doctor

If irritation or redness develops, or if condition persists for more than 72 hours.

Keep out of reach of children

If swallowed, get medical help or contact Poison Control Center right away.

Directions

- adults and children 2 years and over: apply to hands; allow to dry without wiping.
- children under 2 years: ask a doctor before use.

Other information

- store below 95°F (35°C).
- may discolor certain fabrics or surfaces.

Inactive ingredients

Water, Decyl Glucoside, Aloe Barbadensis (Aloe) Leaf Extract, Disodium EDTA, Citric Acid, Phenoxyethanol, Potassium Sorbate, Sodium Benzoate.

Principal Display Panel

NDC 73725-013-60

Nature's Baby

alcohol-free hand sanitizing wipes

fragrance free

97.5% puriﬁed water • softer & more absorbent biodegradable • decomposable

no chlorine phthalates, parabens, or sulfates moisturizing and hypo-allergenic

kills 99.9% of most common harmful germs & bacteria

Individually-wrapped packaging makes it convenient and easy to carry in purse, during travels and elsewhere outside of your home.

Our wipes are formulated to be gentle on skin and do not contain fragrance, dye, triclosan, parabens or phthalates

The 60-count individual wraps fit anywhere, making it convenient to take with you throughout the day while you are on-the-go.

Distributed by Nature's Organics, LLC 1560-1 Newbury Rd., #284
Newbury Park, CA 91320
www.naturesbaby.com
Follow us @ twitter.com/ntrsbabyorganic Like us @ facebook.com
Made in USa

60 Individually Packaged Wipes • 8 in x 6 in (20.32cm x 15.24 cm)